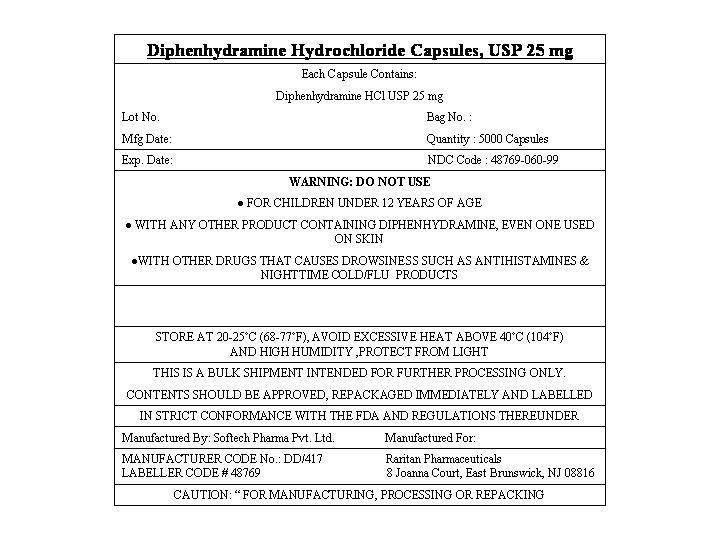 DRUG LABEL: Diphenhydramine HCl
NDC: 48769-060 | Form: CAPSULE, LIQUID FILLED
Manufacturer: Softech Pharma Pvt. Ltd
Category: otc | Type: HUMAN OTC DRUG LABEL
Date: 20121213

ACTIVE INGREDIENTS: DIPHENHYDRAMINE HYDROCHLORIDE 25 mg/1 1
INACTIVE INGREDIENTS: FD&C BLUE NO. 1; FD&C RED NO. 40; GELATIN; GLYCERIN; METHYLPARABEN; POLYETHYLENE GLYCOL 400; PROPYLPARABEN; WATER; SORBITOL; TITANIUM DIOXIDE

Diphenhydramine HCl 25 mg

Active Ingredient in each Softgel

Diphenhydramine HCl 25 mg

Purpose

Nighttime sleep-aid

Uses

- for relief of occassional sleeplessness
- reduces time to fall asleep if you have difficulty falling asleep

Warnings

Do not use

- for children under 12 years of age
- with any other product containing diphenhydramine, even one used on skin
- with other drugs that causes drowsiness such as antihistamines & nighttime cold/flu products

Directions

Take only one dose per day (24 hours) - see Overdose warning

adults & children 12 yrs & over One dose = Two 25 mg Softgels (50 mg) at bedtime if needed or as directed by a doctor

Other Information

- store at 20-25˚C (68-77˚F)
- avoid excessive heat above 40˚C (104˚F) and high humidity
- protect from light

Inactive Ingredients

FD&C blue#1, FD&C red#40, gelatin, glycerin, methylparaben, polyethylene glycol, propylparaben, purified water, sorbitol, titanium dioxide

Principal Display Panel

Diphenhydramine Hydrochloride Capsules, USP 25 mg